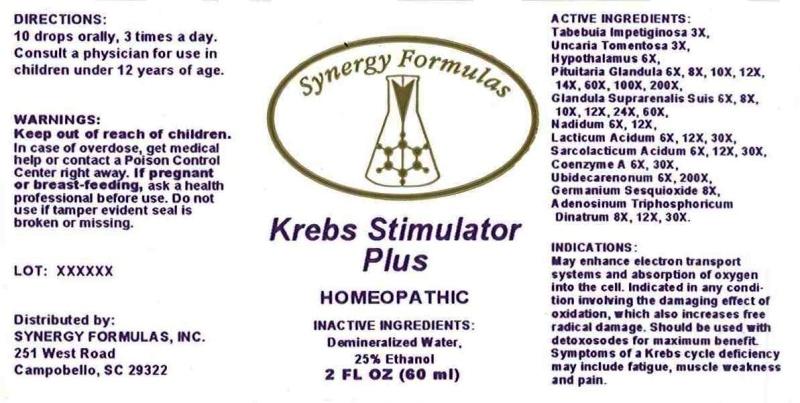 DRUG LABEL: KREBS STIMULATOR PLUS
NDC: 43772-0050 | Form: LIQUID
Manufacturer: Synergy Formulas, Inc.
Category: homeopathic | Type: HUMAN OTC DRUG LABEL
Date: 20151105

ACTIVE INGREDIENTS: TABEBUIA IMPETIGINOSA BARK 3 [hp_X]/1 mL; CAT'S CLAW 3 [hp_X]/1 mL; SUS SCROFA HYPOTHALAMUS 6 [hp_X]/1 mL; SUS SCROFA PITUITARY GLAND 6 [hp_X]/1 mL; SUS SCROFA ADRENAL GLAND 6 [hp_X]/1 mL; NADIDE 6 [hp_X]/1 mL; LACTIC ACID, DL- 6 [hp_X]/1 mL; LACTIC ACID, L- 6 [hp_X]/1 mL; COENZYME A 6 [hp_X]/1 mL; UBIDECARENONE 6 [hp_X]/1 mL; GERMANIUM SESQUIOXIDE 8 [hp_X]/1 mL; ADENOSINE TRIPHOSPHATE DISODIUM 8 [hp_X]/1 mL
INACTIVE INGREDIENTS: WATER; ALCOHOL

DRUG FACTS:

ACTIVE INGREDIENTS:

Tabebuia Impetiginosa 3X, Uncaria Tomentosa 3X, Hypothalamus (Suis) 6X, Pituitaria Glandula (Suis) 6X, 8X, 10X, 12X, 14X, 60X, 100X, 200X, Glandula Suprarenalis Suis 6X, 8X, 10X, 12X, 24X, 60X, Nadidum 6X, 12X, Lacticum Acidum 6X, 12X, 30X, Sarcolacticum Acidum 6X, 12X, 30X, Coenzyme A 6X, 30X, Ubidecarenonum 6X, 200X, Germanium Sesquioxide 8X, Adenosinum Triphosphoricum Dinatrum 8X, 12X, 30X.

INDICATIONS:

May enhance electron transport systems and absorption of oxygen into the cell. Indicated in any condition involving the damaging effect of oxidation, which also increases free radical damage. Should be used with detoxosodes for maximum benefit. Symptoms of a Krebs cycle deficiency may include fatigue, muscle weakness and pain.

WARNINGS:

Keep out of reach of children. In case of overdose, get medical help or contact a Poison Control Center right away.

If pregnant or breast-feeding, ask a health professional before use.

Do not use if tamper evident seal is broken or missing.

Keep out of reach of children. In case of overdose, get medical help or contact a Poison Control Center right away.

DIRECTIONS:

10 drops orally, 3 times a day. Consult a physician for use in children under 12 years of age.

INDICATIONS:

May enhance electron transport systems and absorption of oxygen into the cell. Indicated in any condition involving the damaging effect of oxidation, which also increases free radical damage. Should be used with detoxosodes for maximum benefit. Symptoms of a Krebs cycle deficiency may include fatigue, muscle weakness and pain.

INACTIVE INGREDIENTS:

Demineralized Water, 25% Ethanol

QUESTIONS:

Distributed by:

SYNERGY FORMULAS, INC.

251 West Road

Campobello, SC 29322

PACKAGE LABEL DISPLAY:

Synergy Formulas

Krebs Stimulator
Plus

HOMEOPATHIC
2 FL OZ (60 ml)